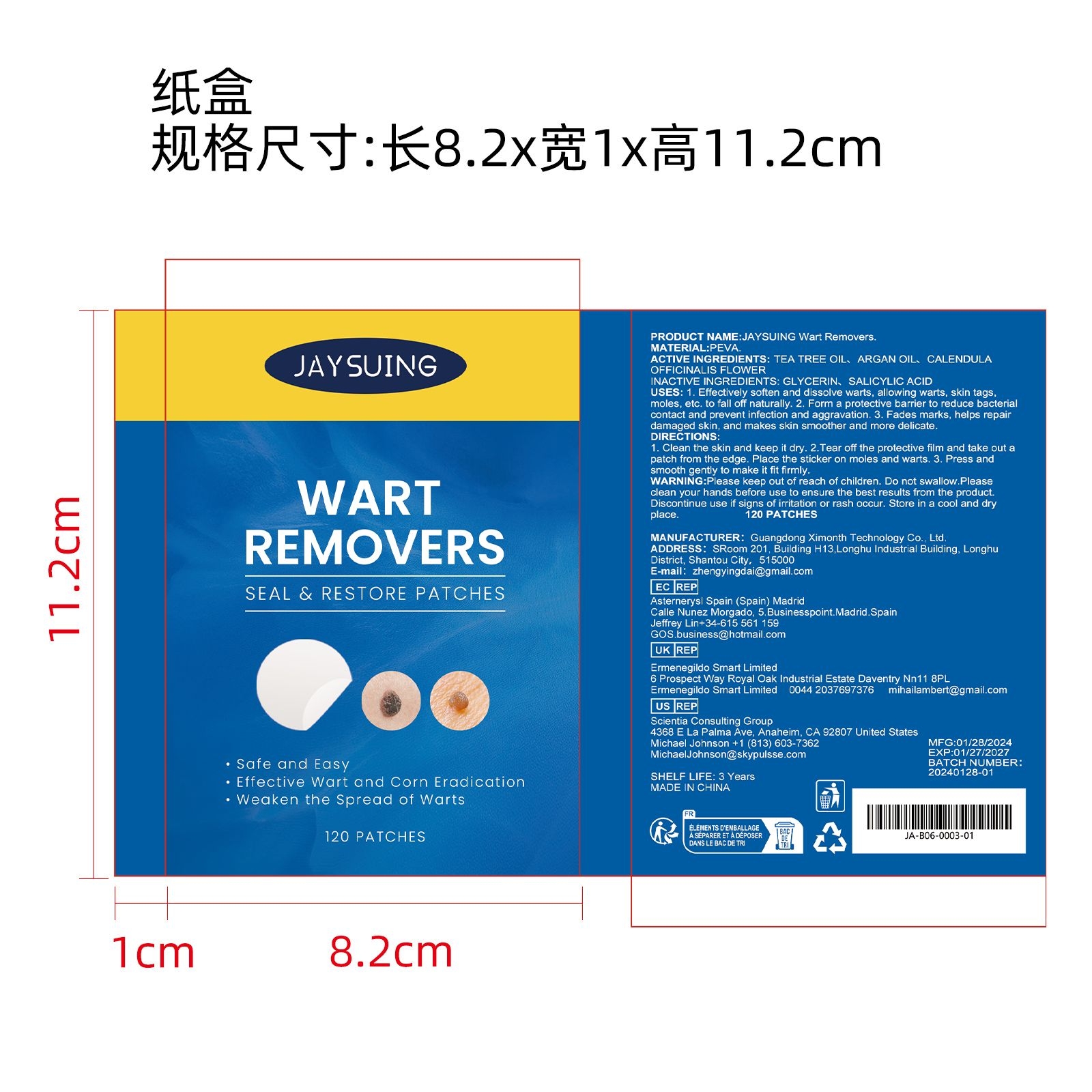 DRUG LABEL: JAYSUING Wart Removers
NDC: 84660-055 | Form: PATCH
Manufacturer: Guangdong Ximonth Technology Co., Ltd.
Category: otc | Type: HUMAN OTC DRUG LABEL
Date: 20241031

ACTIVE INGREDIENTS: TEA TREE OIL 2 g/12 g; ARGAN OIL 2 g/12 g; CALENDULA OFFICINALIS FLOWER 4 g/12 g
INACTIVE INGREDIENTS: SALICYLIC ACID 2 g/12 g; GLYCERIN 2 g/12 g

Active Ingredient(s)

ACTIVE INGREDIENTS： TEA TREE OIL、ARGAN OIL、CALENDULA OFFICINALIS FLOWER

Purpose

1. Effectively soften and dissolve warts, allowing warts, skin tags, moles, etc. to fall off naturally.
2. Form a protective barrier to reduce bacterial contact and prevent infection and aggravation.
3. Fades marks, helps repair damaged skin, and makes skin smoother and more delicate.

Use

1. Clean the skin and keep it dry.
2.Tear off the protective film and take out a patch from the edge. Place the sticker on moles and warts.
3. Press and smooth gently to make it fit firmly.

Warnings

Please keep out of reach of children.Do not swallow.Please clean your hands before use to ensure the best results from the product.Discontinue use if signs of irritation or rash occur.Store in a cool and dry place.

Do not use

Discontinue use if signs of irritation or rash occur.

Stop Use

Discontinue use if signs of irritation or rash occur.

KEEP OUT OF REACH OF CHILDREN

Please keep out of reach of children. Do not swallow.

STORAGE AND HANDLING

Store in a cool and dry place.

INACTIVE INGREDIENTS：GLYCERIN、SALICYLIC ACID